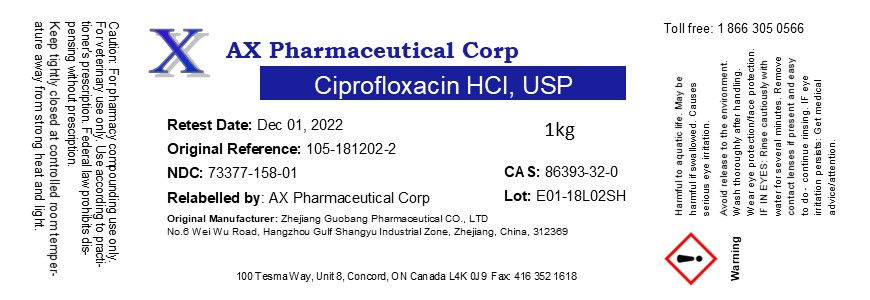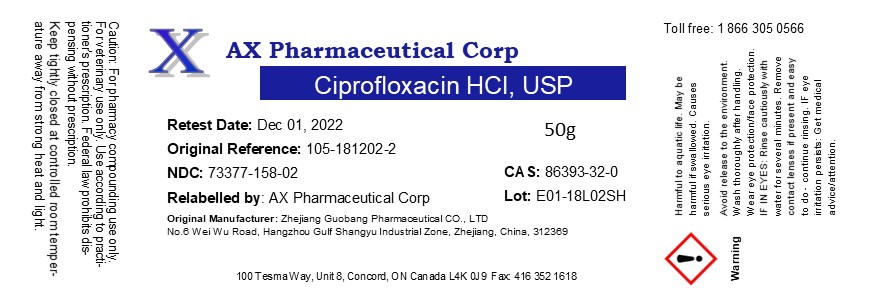 DRUG LABEL: Ciprofloxacin Hydrochloride
NDC: 73377-158 | Form: POWDER
Manufacturer: AX Pharmaceutical Corp
Category: other | Type: BULK INGREDIENT - ANIMAL DRUG
Date: 20260119

ACTIVE INGREDIENTS: CIPROFLOXACIN HYDROCHLORIDE 1 g/1 g

Ciprofloxacin Hydrochloride